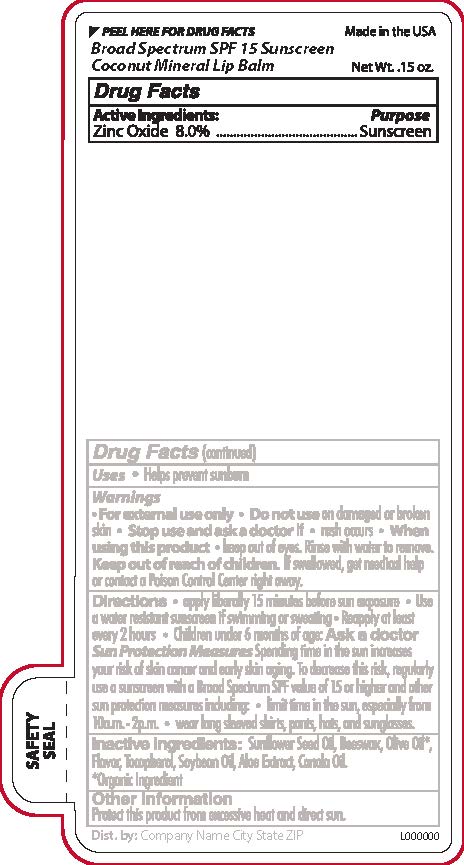 DRUG LABEL: Coconut Mineral SPF 15 Broad Spectrum Lip Balm
NDC: 65692-0558 | Form: STICK
Manufacturer: Raining Rose, Inc
Category: otc | Type: HUMAN OTC DRUG LABEL
Date: 20231023

ACTIVE INGREDIENTS: ZINC OXIDE 0.34 g/4.25 g
INACTIVE INGREDIENTS: CANOLA OIL; SUNFLOWER OIL; TOCOPHEROL; WHITE WAX; OLIVE OIL; ALOE VERA LEAF; SOYBEAN OIL

Coconut SPF 15 Mineral Lip Balm

Active Ingredients

Avobenzone 2.0%

Octinoxate 6.5%

Octisalate 5.0%

Octocrylene 1.5%

Purpose

Sunscreen

Warnings

For external use only

Do not use

on damaged or broken skin.

Stop Use and ask a doctor if

Rash Occurs

When Using this Product

Keep out of eyes. Rinse well with water to remove.

Keep out of reach of children

If swallowed, get medical help or contact a Poison Control Center right away.

Directions

Apply liberally 15 minutes before sun exposure

Use a water resistant sunscreen if swimming or sweating

Reapply at least every 2 hours
Children under 6 months of age: Ask a doctor

Inactive ingredients:

Sunflower Seed Oil*, Beeswax, Olive Oil*, Flavor, Tocopherol, Soybean Oil, Aloe Extract, Canola Oil. * Organic

DOSAGE AND ADMINISTRATION

Apply liberally 15 minutes before sun exposure

INDICATIONS AND USAGE

Helps prevent sunburn